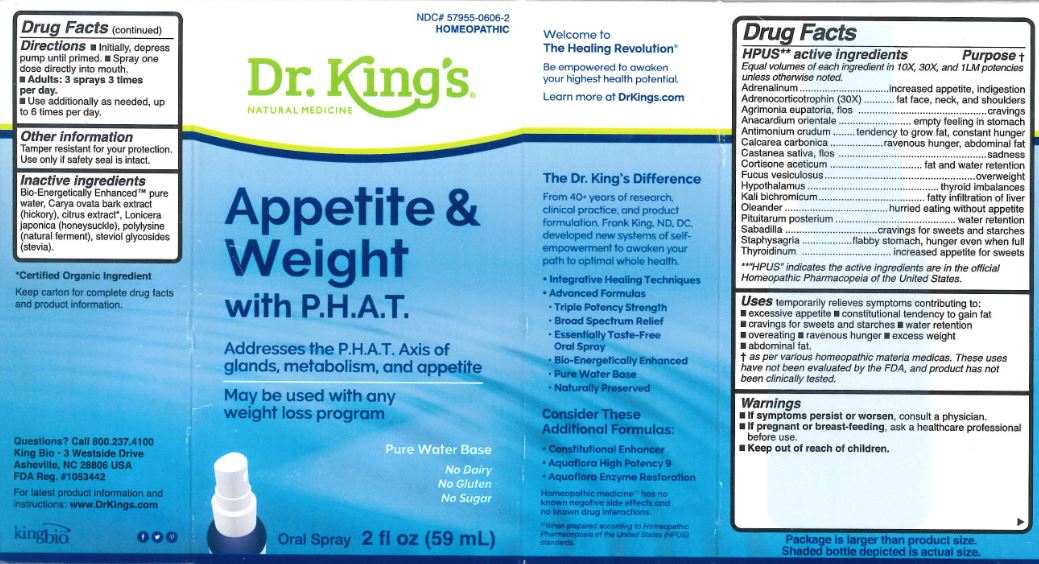 DRUG LABEL: Appetite and Weight with P.H.A.T.
NDC: 57955-0606 | Form: LIQUID
Manufacturer: King Bio Inc.
Category: homeopathic | Type: HUMAN OTC DRUG LABEL
Date: 20180223

ACTIVE INGREDIENTS: EPINEPHRINE 10 [hp_X]/59 mL; CORTICOTROPIN 30 [hp_X]/59 mL; AGRIMONIA EUPATORIA FLOWER 10 [hp_X]/59 mL; SEMECARPUS ANACARDIUM JUICE 10 [hp_X]/59 mL; ANTIMONY TRISULFIDE 10 [hp_X]/59 mL; OYSTER SHELL CALCIUM CARBONATE, CRUDE 10 [hp_X]/59 mL; CASTANEA SATIVA FLOWER 10 [hp_X]/59 mL; CORTISONE ACETATE 10 [hp_X]/59 mL; FUCUS VESICULOSUS 10 [hp_X]/59 mL; BOS TAURUS HYPOTHALAMUS 10 [hp_X]/59 mL; POTASSIUM DICHROMATE 10 [hp_X]/59 mL; NERIUM OLEANDER LEAF 10 [hp_X]/59 mL; SUS SCROFA PITUITARY GLAND 10 [hp_X]/59 mL; SCHOENOCAULON OFFICINALE SEED 10 [hp_X]/59 mL; DELPHINIUM STAPHISAGRIA SEED 10 [hp_X]/59 mL; THYROID, UNSPECIFIED 10 [hp_X]/59 mL
INACTIVE INGREDIENTS: WATER; CITRIC ACID MONOHYDRATE; POTASSIUM SORBATE

Appetite and Weitht with P.H.A.T.

ACTIVE INGREDIENT

Drug Facts__________________________________________________________________________________________________________

HPUS active ingredients: Adrenalinum, Adrenocorticotrophin (30X), Agrimonia eupatoria, flos, Anacardium orientale, Antimonium crudum, Calcarea carbonica, Castanea sativa, flos, Cortisone aceticum, Fucus vesiculosus, Hypothalamus, Kali bichromicum, Oleander, Pituitarum posterium, Sabadilla, Staphysagria, Thyroidinum.

Equal volumes of each ingredient in 10X, 30X, and 1LM potencies.

INDICATIONS AND USAGE

Uses temporarily relieves symptoms contributing to: excessive appetite, constitutional tndency to gain fat, overeating, cravings for sweets and starches, water retention, excess weight, abdominal fat.

Inactive Ingredients:

Bio-Energetically Enhanced™ pure water, Carya ovata bark extract (hickory), citrus extract, Lonicera japonica (honeysuckle), polylysine (natural ferment), steviol glycosides (stevia).

Warnings

- If symptoms persist or worsen, consult a physician.
- If pregnant or breast-feeding, ask a healthcare professional before use.

- Keep out of reach of children.

Directions

- Initially, depress pump until primed.
- Spray one dose directly into mouth.
- Adults: 3 sprays 3 times per day.
- Use additionally as needed, up to 6 times per day.

OTHER SAFETY INFORMATION

Tamper resistant for your protection. Use only if safety seal is intact.

PURPOSE

Adrenalinum...increased appetite, indigestion

Adrenocorticotrophin (30X)...fat face, neck, and shoulders

Agrimonia eupatoria, flos......cravings

Anacardium orientale....empty feeling in stomach

Antimonium crudum...tendency to grow fat, constant hunger

Calcarea carbonica....ravenous hunger, abdominal fat

Castanea sativa, flos......sadness

Cortisone aceticum.....fat and water retention

Fucus vesiculosus......overweight

Hypothalamus.....thyroid imbalances

Kali bichromicum.........fatty infiltration of liver

Oleander......hurried eating without appetite

Pituitarum posterium.....water retention

Sabadilla.....cravings for sweets and starches

Staphysagria......flabby stomach

Thyroidinum......increased appetite for sweets.